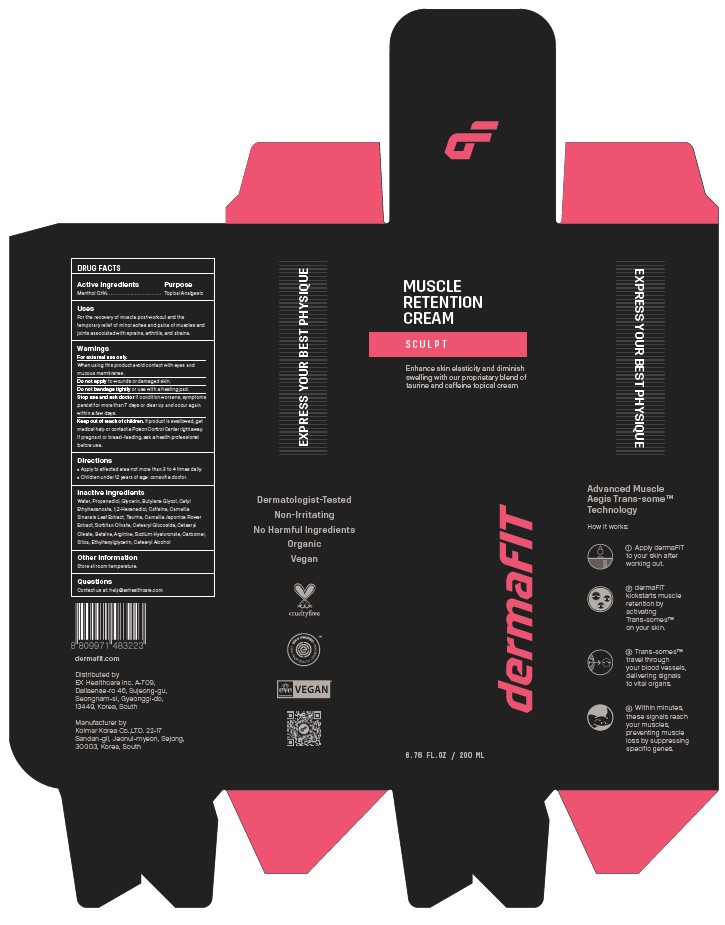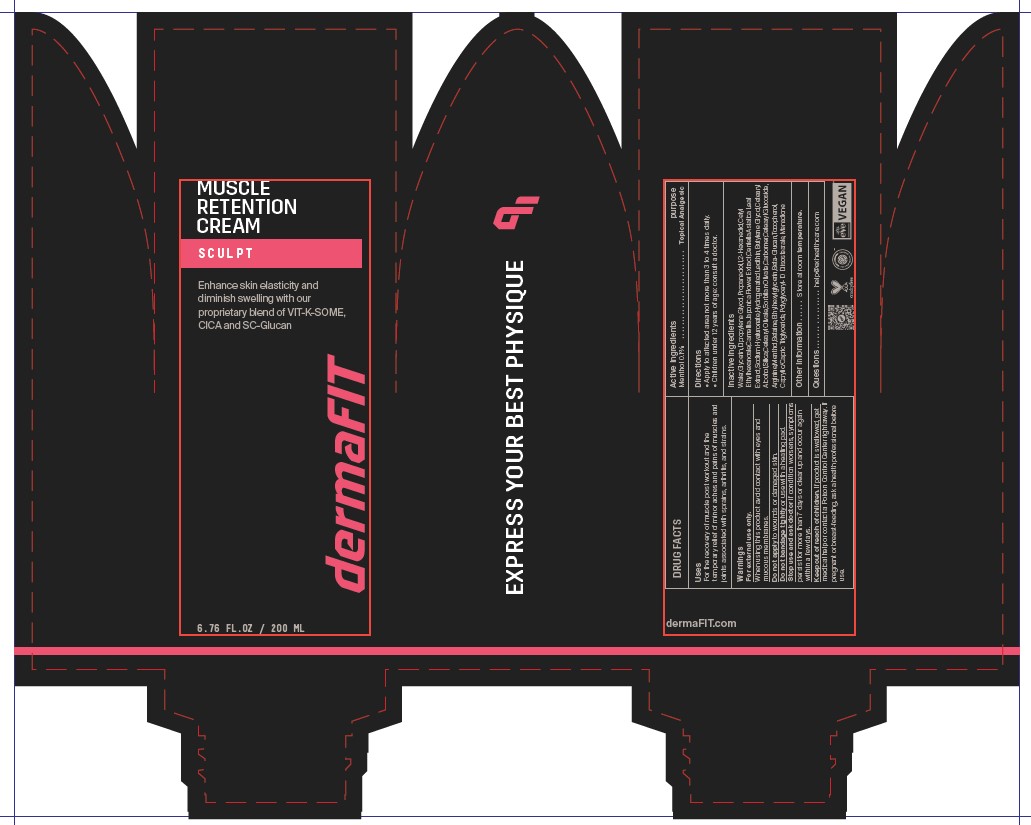 DRUG LABEL: dermaFIT Muscle Retention Cream Sculpt
NDC: 82679-113 | Form: CREAM
Manufacturer: EX Healthcare Inc.
Category: otc | Type: HUMAN OTC DRUG LABEL
Date: 20260223

ACTIVE INGREDIENTS: MENTHOL 0.1 g/200 mL
INACTIVE INGREDIENTS: POLYGLYCERYL-10 DIISOSTEARATE; GLYCERIN; DIPROPYLENE GLYCOL; PROPANEDIOL; CETYL ETHYLHEXANOATE; 1,2-HEXANEDIOL; BUTYLENE GLYCOL; CETEARYL ALCOHOL; SILICA; CETEARYL OLIVATE; SORBITAN OLIVATE; CARBOMER; ARGININE; CETEARYL GLUCOSIDE; BETAINE; ETHYLHEXYLGLYCERIN; SODIUM HYALURONATE; TOCOPHEROL; CAPRYLIC/CAPRIC TRIGLYCERIDE; MENADIONE; HYDROGENATED SOYBEAN LECITHIN; CENTELLA ASIATICA LEAF; AQUA

dermaFIT Muscle Retention Cream Sculpt

ACTIVE INGREDIENT

MENTHOL 0.1%

PURPOSE

Topical Analgesic

INDICATIONS AND USAGE

For the recovery of muscle post workout and the
temporary relief of minor aches and pains of muscles and
joints associated with sprains, arthritis, and strains.

WARNINGS

For external use only.

DO NOT USE

to wounds or damaged skin.

When using this product avoid contact with eyes and
mucous membranes.

STOP USE

if condition worsens, symptoms
persist for more than 7 days or clear up and occur again
within a few days.

KEEP OUT OF REACH OF CHILDREN

If product is swallowed, get
medical help or contact a Poison Control Center right away.
If pregnant or breast-feeding, ask a health professional
before use.

INACTIVE INGREDIENT

Water, Propanediol, Glycerin, Butylene Glycol, Cetyl
Ethylhexanoate, 1,2-Hexanediol, Camellia Japonica Flower
Extract, Sorbitan Olivate, Cetearyl Glucoside, Cetearyl
Olivate, Betaine, Arginine, Sodium Hyaluronate, Carbomer,
Silica, Ethylhexylglycerin, Cetearyl Alcohol

OTHER SAFETY INFORMATION

Store at room temperature.

Directions

• Apply to affected area not more than 3 to 4 times daily.
• Children under 12 years of age: consult a doctor.